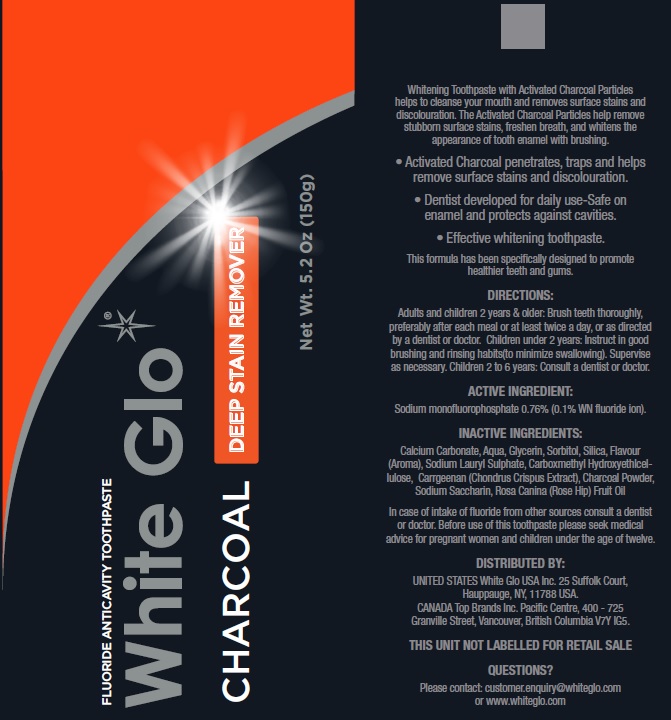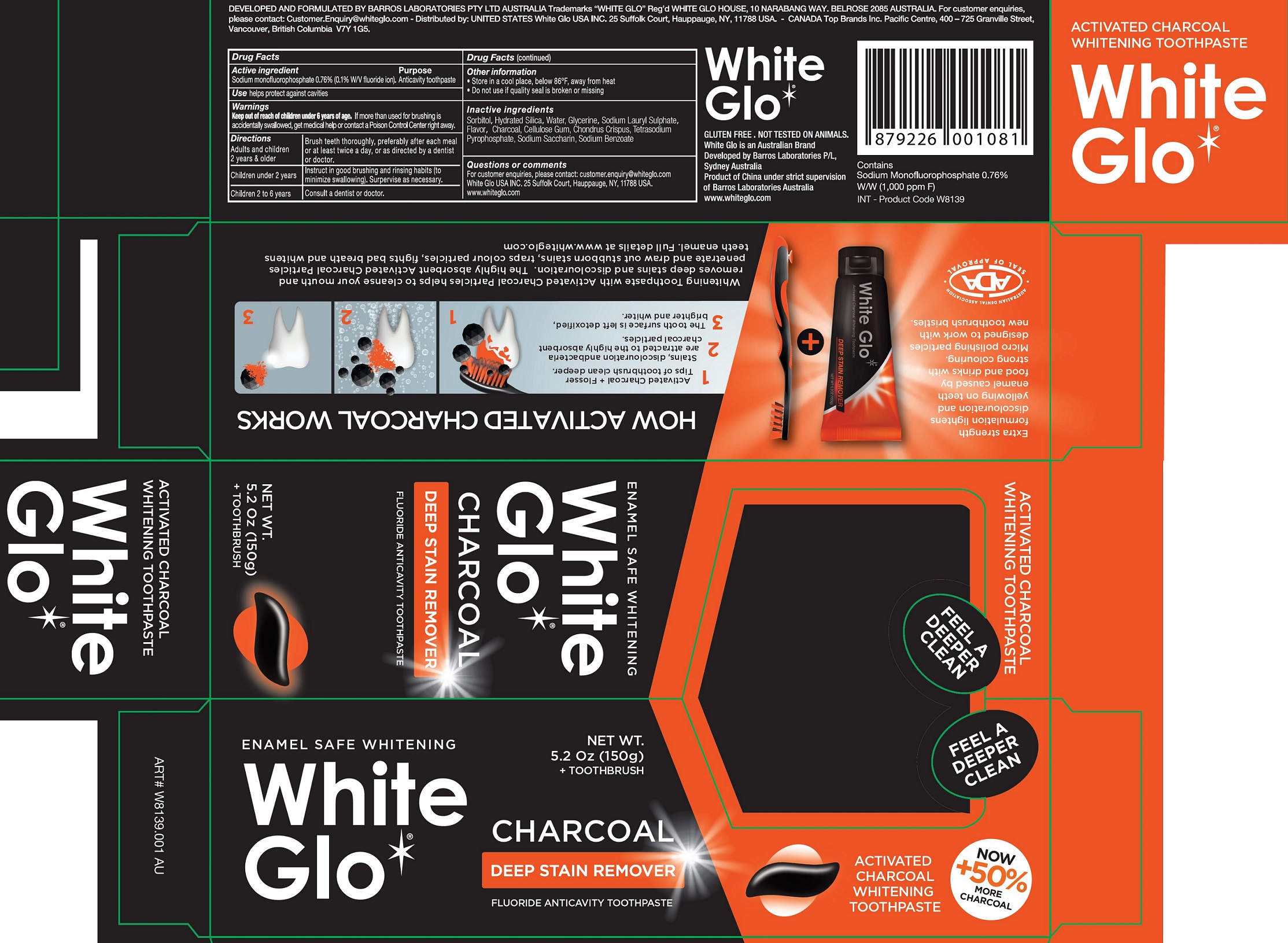 DRUG LABEL: WHITE GLO CHARCOAL
NDC: 73656-009 | Form: KIT | Route: DENTAL
Manufacturer: WHITE GLO USA INC
Category: otc | Type: HUMAN OTC DRUG LABEL
Date: 20250226

ACTIVE INGREDIENTS: SODIUM MONOFLUOROPHOSPHATE 7.6 mg/1 g
INACTIVE INGREDIENTS: SORBITOL; HYDRATED SILICA; WATER; GLYCERIN; SODIUM LAURYL SULFATE; METHYL SALICYLATE; ACTIVATED CHARCOAL; CARBOXYMETHYLCELLULOSE SODIUM, UNSPECIFIED FORM; CHONDRUS CRISPUS; SODIUM PYROPHOSPHATE; SACCHARIN SODIUM; SODIUM BENZOATE

WHITE GLO CHARCOAL Kit

Active ingredient

Sodium monofluorophosphate 0.76% (0.1% W/V fluoride ion)

Purpose

Anticavity toothpaste

Use

helps protect against cavities

Warnings

Keep out of reach of children under 6 years of age.

If more than used for brushing is accidentally swallowed, get medical help or contact a Poison Control Center right away.

Directions

Adults and children 2 years & older | Brush teeth thoroughly, preferably after each meal or at least twice a day, or as directed by a dentist or doctor.
Children under 2 years | Instruct in good brushing and rinsing habits (to minimize swallowing). Supervise children as necessary.
Children 2 to 6 years | Consult a dentist or doctor.

Other information

- Store in a cool place, below 86°F, away from heat
- Do not use if quality seal is broken or missing

Inactive ingredients

Sorbitol, Hydrated Silica, Water, Glycerine, Sodium Lauryl Sulphate, Flavor, Charcoal, Cellulose Gum, Chondrus Crispus, Tetrasodium Pyrophosphate, Sodium Saccharin, Sodium Benzoate

Questions or comments

For customer enquiries, please contact: customer.enquiry@whiteglo.com White Glo USA INC.25 Suffolk Court, Hauppauge, NY, 11788 USA. www.whiteglo.com